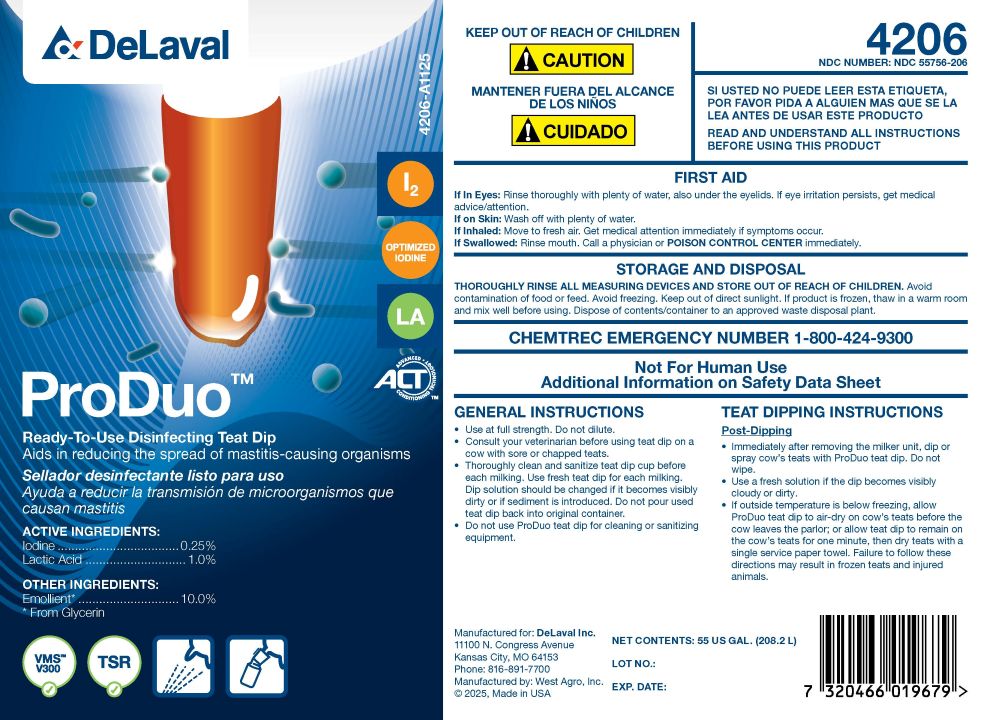 DRUG LABEL: ProDuo
NDC: 55756-206 | Form: SOLUTION
Manufacturer: DeLaval
Category: animal | Type: OTC ANIMAL DRUG LABEL
Date: 20260125

ACTIVE INGREDIENTS: IODINE 2.5 g/1 L; LACTIC ACID 10 g/1 L
INACTIVE INGREDIENTS: WATER; GLYCERIN; XANTHAN GUM; POLOXAMER 335; POLOXAMER 403; C9-11 PARETH-8; SODIUM IODIDE; SODIUM HYDROXIDE; SODIUM IODATE; SODIUM CHLORIDE

ProDuo™

PURPOSE

Ready-To-Use Disinfecting Teat Dip

Aids in reducing the spread of mastitis-causing organisms

ACTIVE INGREDIENTS:

Iodine ................................. 0.25%

Lactic Acid ........................... 1.0%

Other Ingredients:

Emollient*.............................10.%

*From Glycerin

KEEP OUT OF REACH OF CHILDREN

! Caution

PRECAUTIONS

READ AND UNDERSTAND ALL INSTRUCTIONS BEFORE USING THIS PRODUCT

FIRST AID

If in Eyes: Rinse thoroughly with plenty of water, also under the eyelids. If eye irritation persists, get medical advice/attention.

If on Skin: Wash off with plenty of water.

If Inhaled: Move to fresh air. Get medical attantion imppediately if symptoms occur.

If Swallowed: Rinse mouth. Call a physician or POISON CONTROL CENTER immediately.

STORAGE AND DISPOSAL

THOROUGHLY RINSE ALL MEASURING DEVICES AND STORE OUT OF REACH OF CHILDREN. Avoid contamination of food or feed. Avoid freezing. Keep out of direct sunlight. If product is frozen, thaw in a warm room and mix well before using. Dispose of contents/container to an approved waste disposal plant.

PRECAUTIONS

CHEMTREC EMERGENCY NUMBER 1-800-424-9300

Not For Human Use

Additional Information on Safety Data Sheet

GENERAL INSTRUCTIONS

- Use at full strength. Do not dilute.
- Consult your veterinarian before using teat dip on a cow with sore or chapped teats.
- Thoroughly clean and sanitize teat dip cup before each milking. Use fresh teat dip for each milking. Dip solution should be changed if it becomes visibly dirty or if sediment is introduced. Do not pour used teat dip back into original container.
- Do not use ProDuo teat dip for cleaning or sanitizing equipment.

TEAT DIPPING INSTRUCTIONS

Post-Dipping

- Immediately after removing the milker unit, dip or spray cow's teats with ProDuo teat dip. Do not wipe.
- Use a fresh solution if the dip becomes visibly cloudy or dirty.
- If outside temperature is below freezing, allow ProDuo teat dip to air-dry on cow's teats before the cow leaves the parlor; or allow teat dip to remain on the cow's teats for one minute, then dry teats with a single service paper towel. Failure to follow these directions may result in frozen teats and injured animals.

Manufactured for: DeLaval Inc.

11100 N. Congress Avenue

Kansas City, MO 64153

Phone: 1-816-891-7700

Manufactured by: West Agro, Inc.

© 2025 Made in USA